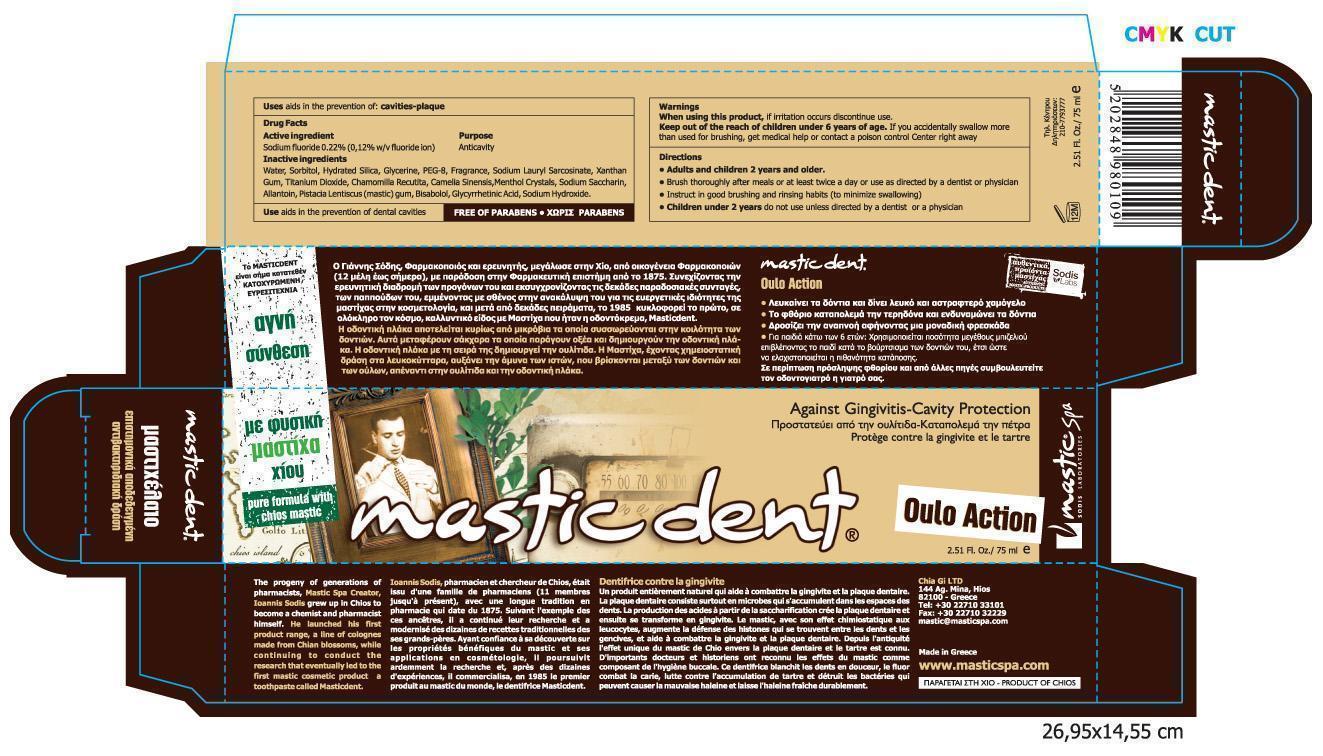 DRUG LABEL: Mastic Dent Oulo Action
NDC: 15304-4681 | Form: PASTE, DENTIFRICE
Manufacturer: Chia Gi LTD
Category: otc | Type: HUMAN OTC DRUG LABEL
Date: 20121226

ACTIVE INGREDIENTS: SODIUM FLUORIDE 2.2 mg/1 mL
INACTIVE INGREDIENTS: ENOXOLONE; POLYETHYLENE GLYCOL 400; SODIUM HYDROXIDE; ALLANTOIN; SORBITOL; GLYCERIN; SODIUM LAUROYL SARCOSINATE; SACCHARIN SODIUM; TITANIUM DIOXIDE; XANTHAN GUM; CAMELLIA SINENSIS SEED OIL; MENTHOL; PISTACIA LENTISCUS RESIN; HYDRATED SILICA; .ALPHA.-BISABOLOL, ()-; CHAMOMILE

Active Ingredients

Drug Facts:

Active Ingredients:

- Sodium Fluoride 0.22% (0.12% w/v fluoride ion) - Anticavity

Warnings

- When using this product, if irritation occurs discontinue use.
- Keep out of reach of children under 6 years of age. If you accidentally swallow more than used for brushing, get medical help or contact a poison control Center right away.

Dosage

Use a pea-sized amount

Keep out of reach of children under 6 years of age.

Directions

- Adults and children 2 years and older.
- Brush thoroughly after meals or at least twice a day or use as directed by a dentist or physician.
- Instruct in good brushing and rinsing habits (to minimize swallowing).
- Children under 2 years do not use unless directed by a dentist or a physician.

Inactive Ingredients

Water, Sorbitol, Hydrated Silica, Glycerine, Peg-8, Fragrance, Sodium Lauryl Sarcosinate, Xanthan Gum, Titanium Dioxide, Chamomilla Recutita, Camelia Sinensis, Menthol Crystals, Sodium Saccharin, Allantoin, Pistacia Lentiscus (Mastic) Gum, Bisabolol, Glycyrrhetinic Acid, Sodium Hydroxide

Information of owner

Product Of Chios

CHIA GI LTD

144 AG. MINA, HIOS, 82100

GREECE
Tel.: 30-22710-33101, FAX: 30-22710-32229
www.masticspa.com
Made In Greece

PURPOSE SECTION

Aids in the prevention of dental cavities